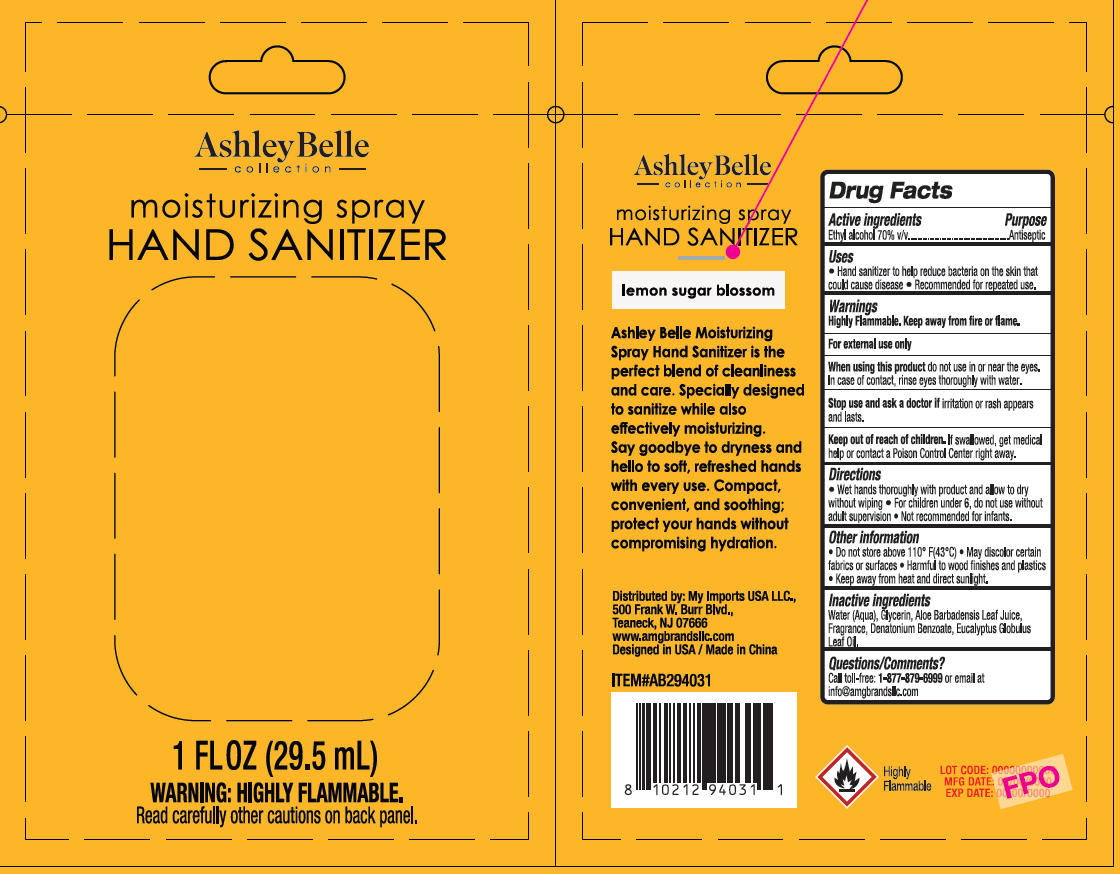 DRUG LABEL: AshleyBelle Moisturizing Hand Sanitizer Lemon Sugar Blossom
NDC: 51628-4535 | Form: SPRAY
Manufacturer: MY IMPORTS USA LLC
Category: otc | Type: HUMAN OTC DRUG LABEL
Date: 20260121

ACTIVE INGREDIENTS: ALCOHOL 70 mL/100 mL
INACTIVE INGREDIENTS: WATER; ALOE BARBADENSIS LEAF JUICE; DENATONIUM BENZOATE; GLYCERIN; EUCALYPTUS GLOBULUS LEAF OIL

AshleyBelle Moisturizing Spray Hand Sanitizer Lemon Sugar Blossom

Active ingredient

Ethyl Alcohol 70% V/V

Uses

- Hand sanitizer to help reduce bacteria on the skin that could cause disease
- Recommended for repeated use.

Warnings

Highly Flammable. Keep away from fire or flame.

For external use only.

When using this product do not use in or near the eyes.

In case of contact, rinse eyes thoroughly with water.

Stop use and ask a doctor if irritation or rash appears and lasts.

Keep out of reach of children

If swallowed, get medical help or contact a Poison Control Center right away.

Directions

- Wet hands thoroughly with product and allow to dry without wiping.
- For children under 6, do not use without adult supervision
- Not recommended for infants.

Other information

- Do not store above 110ºF (43ºC)
- May discolor certain fabrics or surfaces
- Harmful to wood finishes and plastics
- Keep away from heat and direct sunlight

Inactive ingredients

Water(Aqua)

Glycerin

Aloe Barbadensis Leaf Juice

Fragrance

Denatonium Benzoate

Eucalyptus GlobulusLeaf oil

Purpose

Antiseptic